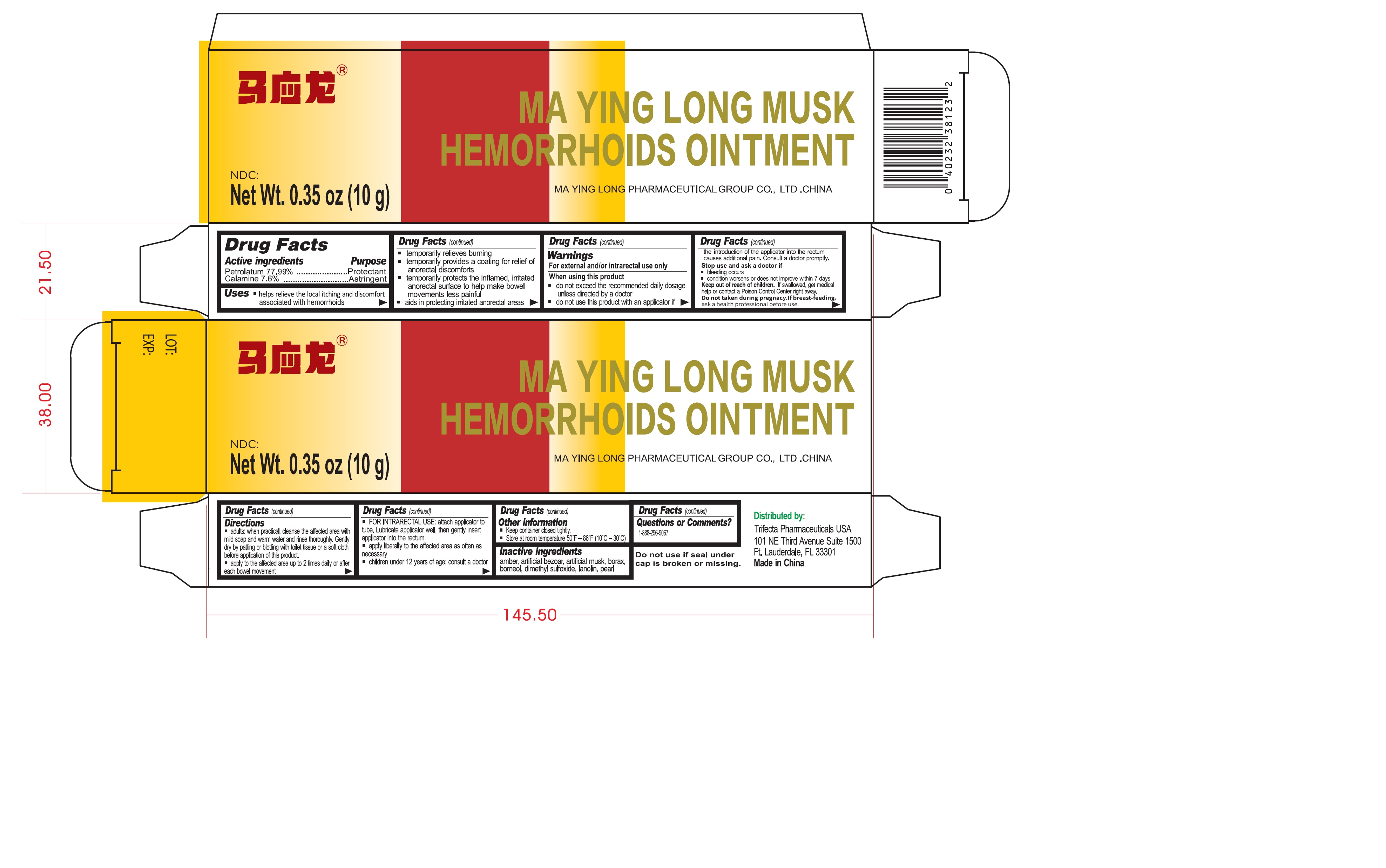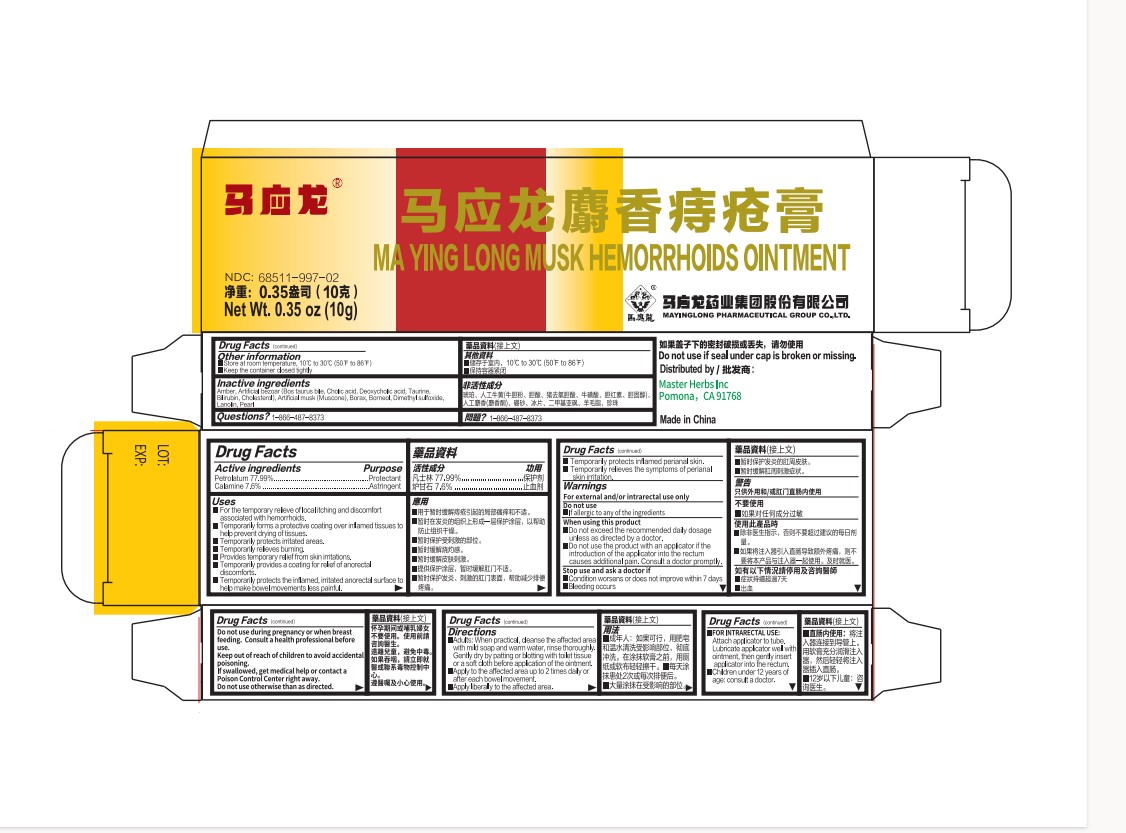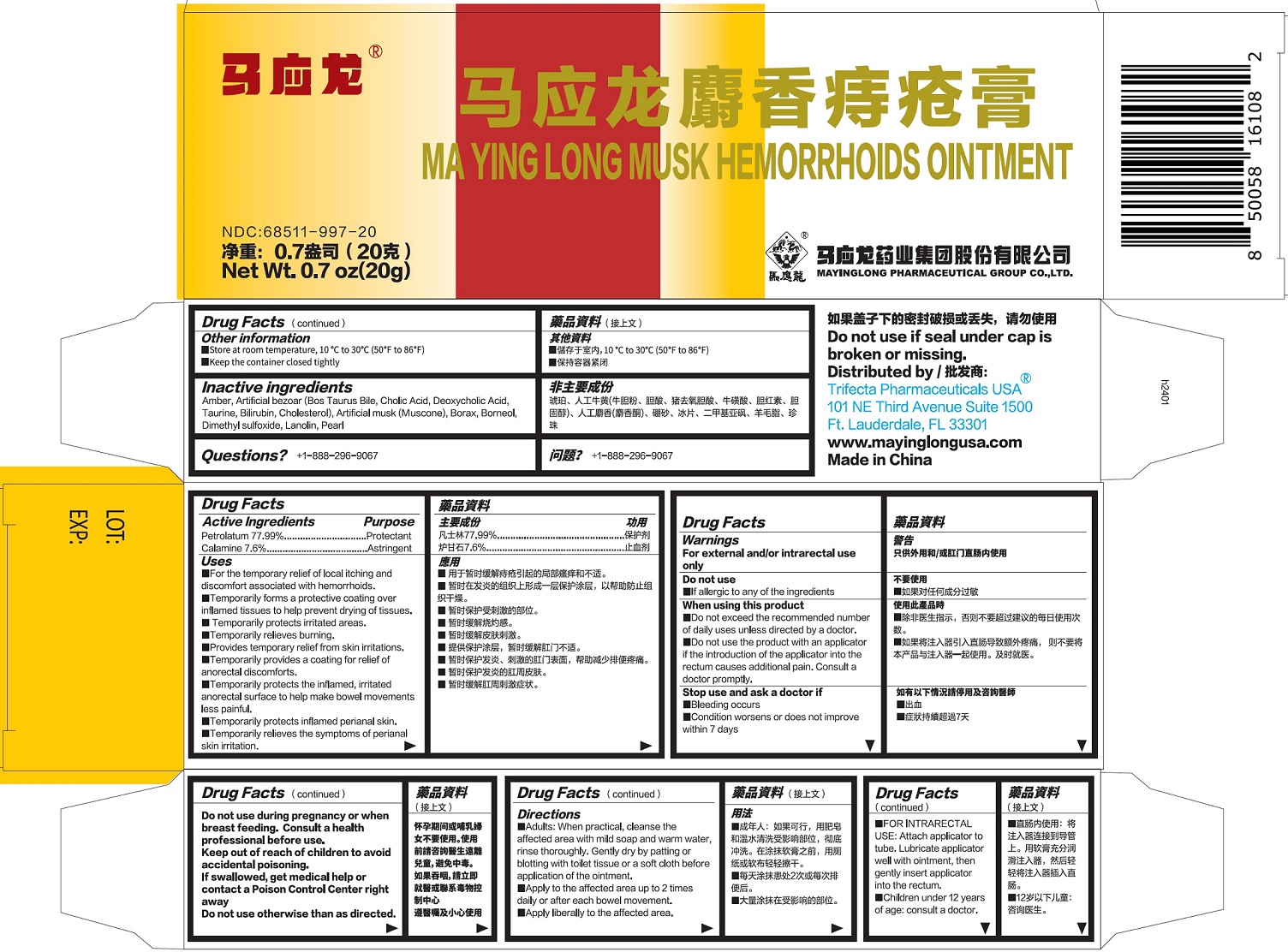 DRUG LABEL: Ma Ying Long Musk Hemorrhoids
NDC: 68511-997 | Form: OINTMENT
Manufacturer: Mayinglong Pharmaceutical Group Co., Ltd.
Category: otc | Type: HUMAN OTC DRUG LABEL
Date: 20240422

ACTIVE INGREDIENTS: PETROLATUM 779.9 mg/1 g; ZINC OXIDE 76 mg/1 g
INACTIVE INGREDIENTS: BOS TAURUS GALLSTONE; AMBER; 6-TERT-BUTYL-3-METHYL-2,4-DINITROANISOLE; SODIUM BORATE; DIMETHYL SULFOXIDE; LANOLIN; PEARL (HYRIOPSIS CUMINGII); BORNEOL

Ma Ying Long Musk Hemorrhoids Ointment

Active ingredients

Petrolatum 77.99% Calamine 7.6%

Purpose

Protectant

Astringent

Uses

- helps relieve the local itching and discomfort associated with hemorrhoids
- temporaily relieves burning
- temporarily provides a coating for relief of anorectal discomforts
- temporarily protects the inflamed, irritated anorectal surface to help make bowel movements less painful
- aids in protecting irritated anorectal areas

Warnings

For external and/or intrarectal use only

When using this product

- do not exceed the recommended daily dosage unless directed by a doctor
- do not use this product with an applicator if the introduction of the applicator into the rectum causes additional pain. Consult a doctor promptly.

Stop use and ask a doctor if

- bleeding occurs
- condition worsens or does not improve within 7 days

Keep out of reach of children.

If swallowed, get medical help or contact a Poison Control Center right away.

Do not taken during pregnacy. If breast-feeding,

ask a health professional before use.

Directions

- adults: when practical, cleanse the affected area with mild soap and warm water and rinse thoroughly. Gently dry by patting or blotting with toilet tissue or a soft cloth before application of this product.
- apply to the affected area up to 2 times daily or after each bowel movement
- FOR INTRARECTAL USE: attach applicator to tube. Lubricant applicator well, then gently insert applicator into the rectum
- apply liberally to the affected area as often as necessary
- children under 12 years of age: consult a doctor

Other information

- Keep container closed tightly.
- Store at room temperature 50°F - 86°F (10°C–30°C)

Inactive ingredients

amber, artificial bezoar, artificial musk, borax, borneol, dimethyl sulfoxide, lanolin, pearl

Questions or Comments?

1-888-296-9067